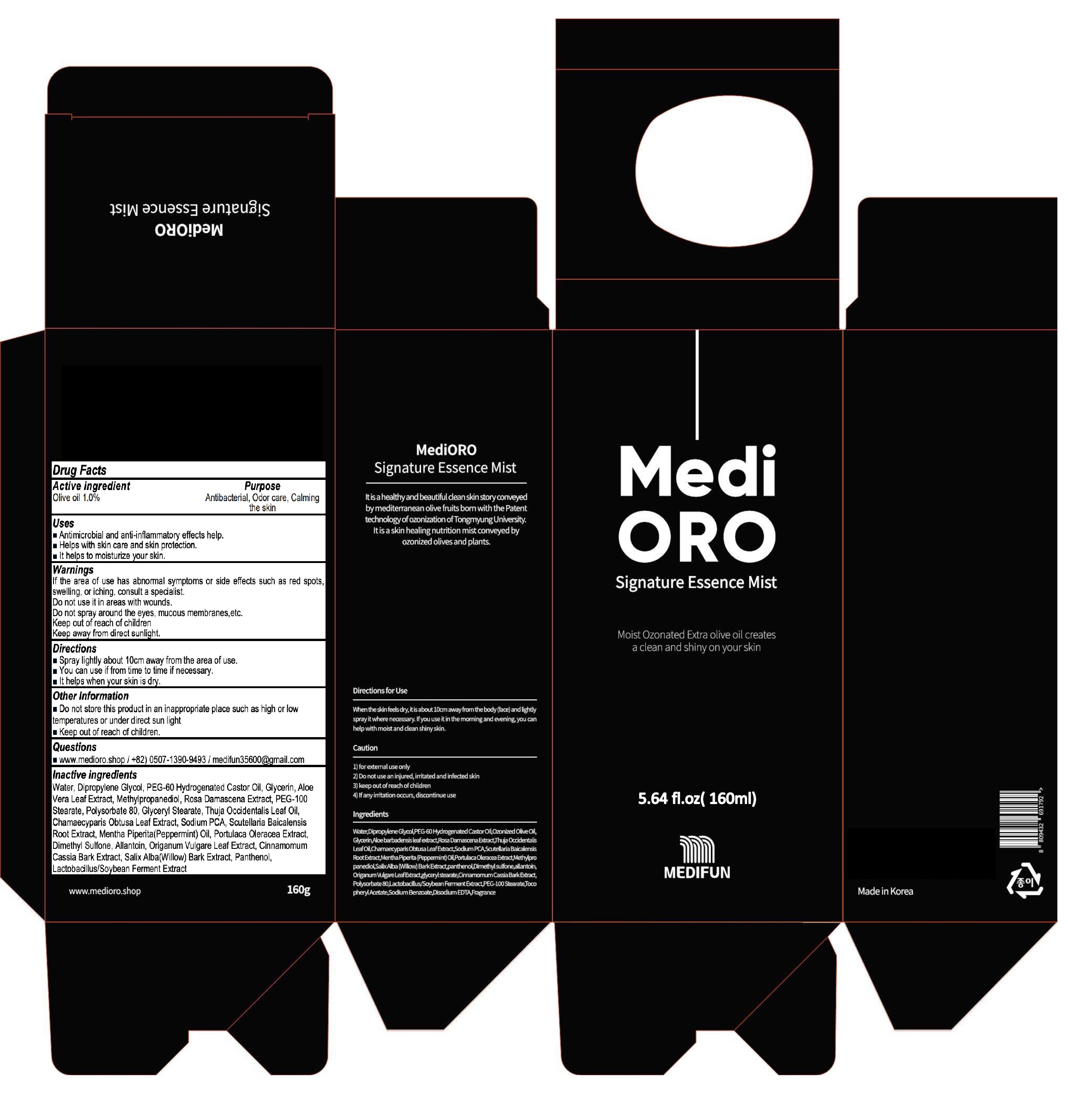 DRUG LABEL: MediORO Signature Essence Mist
NDC: 82363-020 | Form: SPRAY
Manufacturer: MEDIFUN Inc.
Category: otc | Type: HUMAN OTC DRUG LABEL
Date: 20220623

ACTIVE INGREDIENTS: OLIVE OIL 1.60 g/160 mL
INACTIVE INGREDIENTS: Water; Dipropylene Glycol; PEG-60 Hydrogenated Castor Oil

ACTIVE INGREDIENT

Olive oil 1.0%

PURPOSE

Antibacterial, Odor care, Calming the skin

Uses

■ Antimicrobial and anti-inflammatory effects help.
■ Helps with skin care and skin protection.
■ It helps to moisturize your skin.

WARNINGS

If the area of use has abnormal symptoms or side effects such as red spots, swelling, or iching, consult a specialist.
Do not use it in areas with wounds.
Do not spray around the eyes, mucous membranes,etc.
Keep out of reach of children
Keep away from direct sunlight.

KEEP OUT OF REACH OF CHILDREN

Directions

■ Spray lightly about 10cm away from the area of use.
■ You can use if from time to time if necessary.
■ It helps when your skin is dry.

Other Information

■ Do not store this product in an inappropriate place such as high or low temperatures or under direct sun light
■ Keep out of reach of children.

Questions

■ www.medioro.shop / +82) 0507-1390-9493 / medifun35600@gmail.com

INACTIVE INGREDIENTS

Water, Dipropylene Glycol, PEG-60 Hydrogenated Castor Oil, Glycerin, Aloe Vera Leaf Extract, Methylpropanediol, Rosa Damascena Extract, PEG-100 Stearate, Polysorbate 80, Glyceryl Stearate, Thuja Occidentalis Leaf Oil, Chamaecyparis Obtusa Leaf Extract, Sodium PCA, Scutellaria Baicalensis Root Extract, Mentha Piperita(Peppermint) Oil, Portulaca Oleracea Extract, Dimethyl Sulfone, Allantoin, Origanum Vulgare Leaf Extract, Cinnamomum Cassia Bark Extract, Salix Alba(Willow) Bark Extract, Panthenol, Lactobacillus/Soybean Ferment Extract